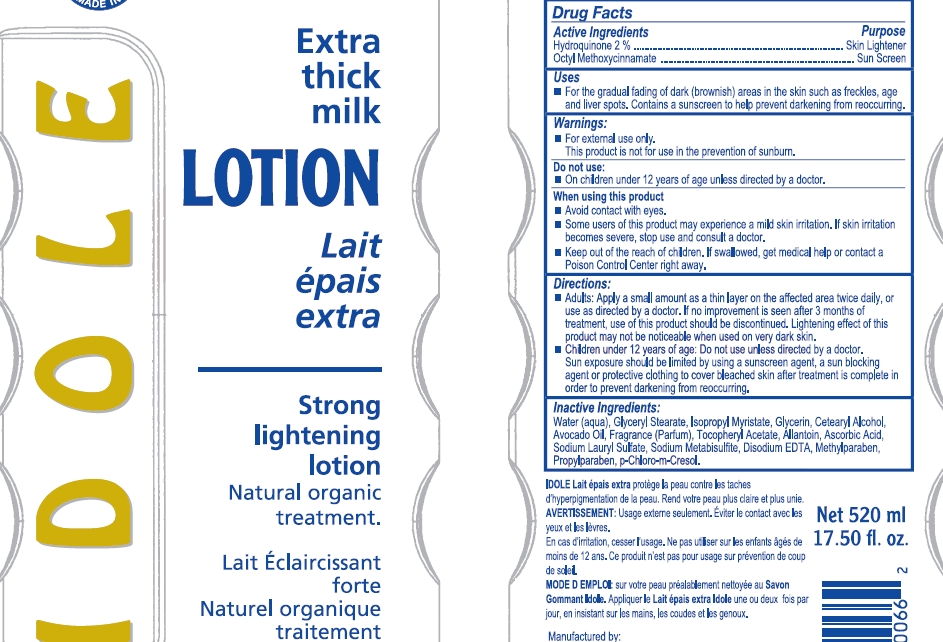 DRUG LABEL: Idole Natural Organic
NDC: 66129-434 | Form: LOTION
Manufacturer: International Beauty Exchange
Category: otc | Type: HUMAN OTC DRUG LABEL
Date: 20120523

ACTIVE INGREDIENTS: HYDROQUINONE 10.4 mL/520 mL; OCTINOXATE 2.6 mL/520 mL
INACTIVE INGREDIENTS: WATER; GLYCERYL STEARATE CITRATE; CETOSTEARYL ALCOHOL; GLYCERIN; ISOPROPYL MYRISTATE; AVOCADO OIL; ALLANTOIN; ASCORBIC ACID; SODIUM METABISULFITE; .ALPHA.-TOCOPHEROL ACETATE, D-; SODIUM LAURYL SULFATE; EDETATE DISODIUM; METHYLPARABEN; PROPYLPARABEN; CHLOROCRESOL

Drug Facts

ACTIVE INGREDIENT

Hydroquinone 2%

Ethylhexyl Methoxycinnamate (Octyl Methoxycinnamate) 0.5%

WARNINGS

For external use only

DO NOT USE

On children under 12 years of age unless directed by a doctor

WHEN USING

Avoid contact with eyes.

PURPOSE

Skin Lightener

INDICATIONS AND USAGE

For the gradual fading of dark (brownish) areas in the skin such as freckles, age and liver spots

DOSAGE AND ADMINISTRATION

Apply a small amount as a thin layer on the affected area twice daily, or use as directed by a doctor

KEEP OUT OF REACH OF CHILDREN

If swallowed, get medical help or contact a Poison Control Center right away

INACTIVE INGREDIENT

WATER,GLYCERYL STEARATE CITRATE, CETOSTEARYL ALCOHOL, GLYCERIN, ISOPROPYL MYRISTATE, ALLANTOIN, ASCORBIC ACID, SODIUM METABISULFITE, .ALPHA.-TOCOPHEROL ACETATE D-, SODIUM LAURYL SULFATE, EDETATE DISODIUM, METHYLPARABEN, PROPYLPARABEN, CHLOROCRESOL